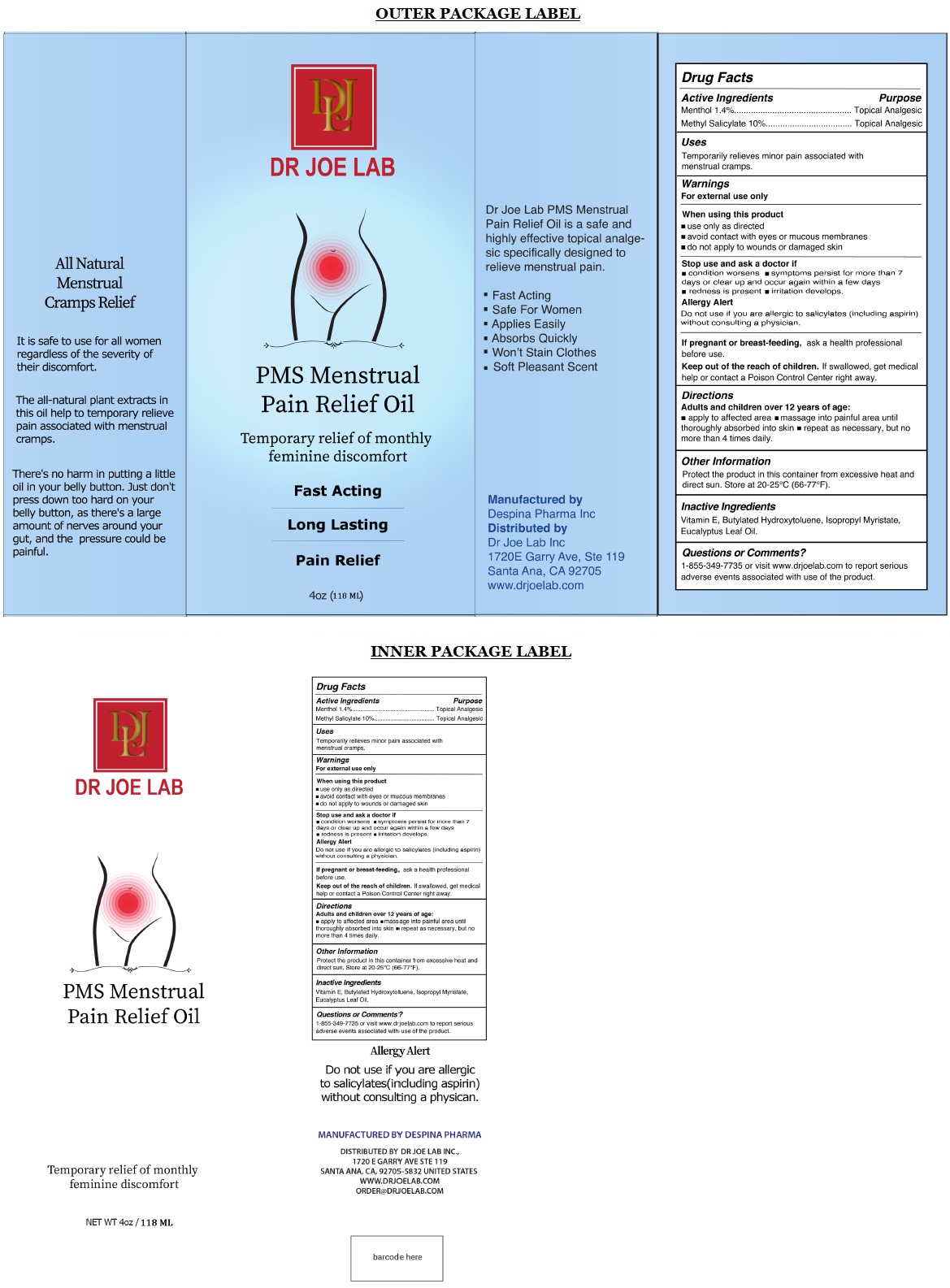 DRUG LABEL: DR JOE LAB PMS Menstrual Pain Relief Oil
NDC: 82331-111 | Form: OIL
Manufacturer: Dr Joe Lab, Inc.
Category: otc | Type: HUMAN OTC DRUG LABEL
Date: 20220407

ACTIVE INGREDIENTS: MENTHOL, UNSPECIFIED FORM 1.4 g/100 mL; METHYL SALICYLATE 10 g/100 mL
INACTIVE INGREDIENTS: .ALPHA.-TOCOPHEROL; BUTYLATED HYDROXYTOLUENE; ISOPROPYL MYRISTATE; EUCALYPTUS OIL

DR JOE LAB PMS Menstrual Pain Relief Oil

Active Ingredients

Menthol 1.4%
Methyl Salicylate 10%

Purpose

Topical Analgesic

Uses

Temporarily relieves minor pain associated with menstrual cramps.

Warnings

For external use only

When using this product
• use only as directed
• avoid contact with eyes or mucous membranes
• do not apply to wounds or damaged skin

Stop use and ask a doctor if
• condition worsens • symptoms persist for more than 7 days or clear up and occur again within a few days • redness is present • irritation develops.

Allergy Alert
Do not use if you are allergic to salicylates (including aspirin) without consulting a physician.

If pregnant or breast-feeding, ask a health professional before use.

KEEP OUT OF REACH OF CHILDREN

Keep out of the reach of children. If swallowed, get medical help or contact a Poison Control Center right away.

Directions

Adults and children over 12 years of age:
• apply to affected area • massage into painful area until thoroughly absorbed into skin • repeat as necessary, but no more than 4 times daily.

Other Information

Protect the product in this container from excessive heat and direct sun. Store at 20-25°C (66-77°F).

Inactive Ingredients

Vitamin E, Butylated Hydroxytoluene, Isopropyl Myristate, Eucalyptus Leaf Oil.

Questions or Comments?

1-855-349-7735 or visit www.drjoelab.com to report serious adverse events associated with use of the product.

Temporary relief of monthly feminine discomfort

Fast Acting

Long Lasting

Pain Relief

Dr Joe Lab PMS Menstrual Pain Relief Oil is a safe and highly effective topical analgesic specifically designed to relieve menstrual pain.

• Fast Acting
• Safe For Women
• Applies Easily
• Absorbs Quickly
• Won’t Stain Clothes
• Soft Pleasant Scent

All Natural Menstrual Cramps Relief

It is safe to use for all women regardless of the severity of their discomfort.

The all-natural plant extracts in this oil help to temporary relieve pain associated with menstrual cramps.

There's no harm in putting a little oil in your belly button. Just don't press down too hard on your belly button, as there's a large amount of nerves around your gut, and the pressure could be painful.

Manufactured by
Despina Pharma Inc
Distributed by
Dr Joe Lab Inc
1720E Garry Ave, Ste 119
Santa Ana, CA 92705
www.drjoelab.com